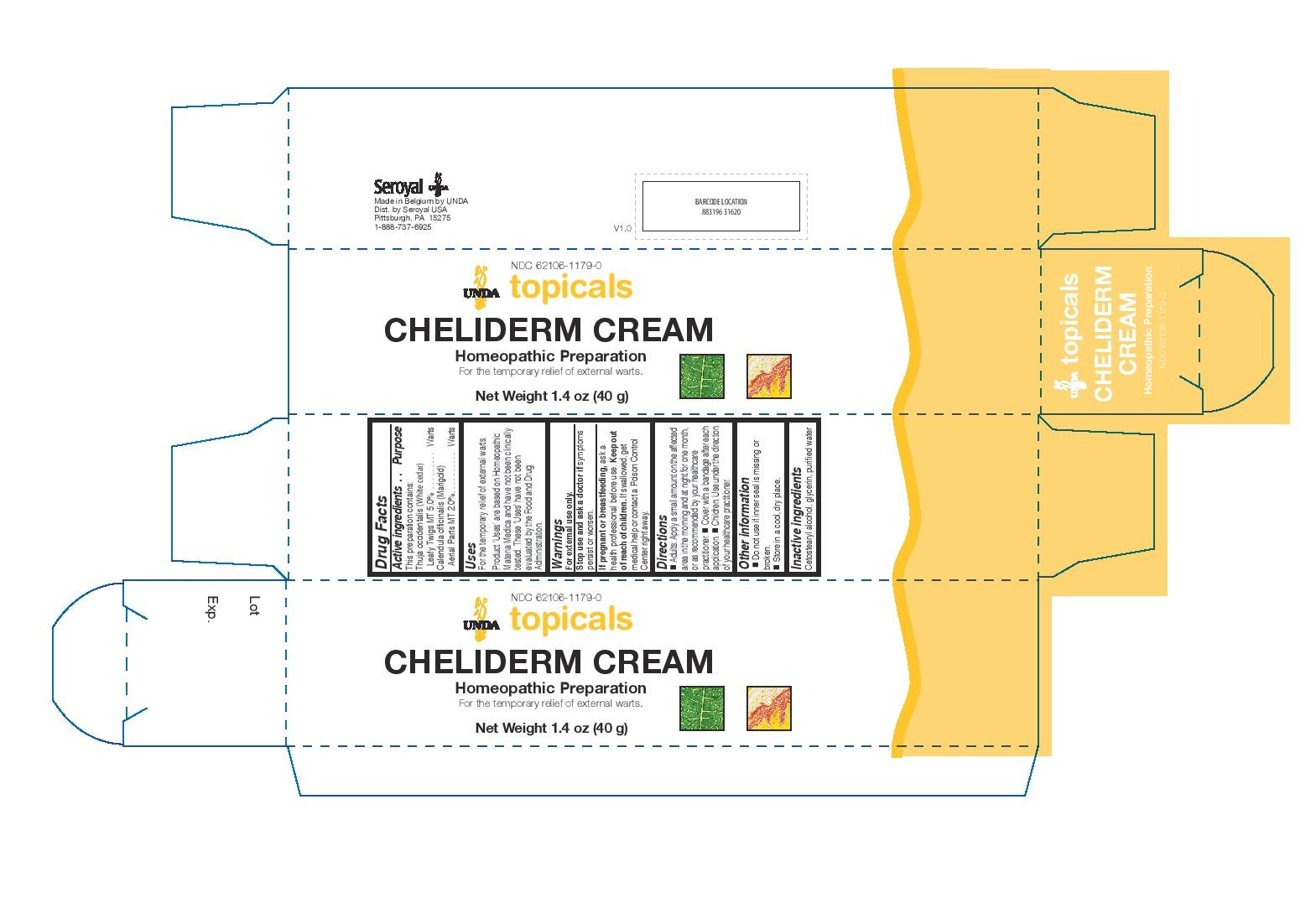 DRUG LABEL: Cheliderm Cream
NDC: 62106-1179 | Form: CREAM
Manufacturer: Seroyal USA
Category: homeopathic | Type: HUMAN OTC DRUG LABEL
Date: 20221109

ACTIVE INGREDIENTS: THUJA OCCIDENTALIS LEAFY TWIG 1 [hp_X]/40 g; CALENDULA OFFICINALIS FLOWERING TOP 1 [hp_X]/40 g
INACTIVE INGREDIENTS: CETOSTEARYL ALCOHOL; GLYCERIN; WATER

CHELIDERM CREAM

Active ingredientse
This preparation contains:
Thuja occidentalis (White cedar) Leafy Twigs MT 5.0%
Calendula officinalis (Marigold) Aerial Parts MT 2.0%

Uses
For the temporary relief of external warts.

Warnings
For external use only.
Stop use and ask a doctor if symptoms
persist or worsen.
If pregnant or breastfeeding, ask a
health professional before use. Keep out
of reach of children. If swallowed, get
medical help or contact a Poison Control
Center right away.

Keep out of reach of children. If swallowed, get
medical help or contact a Poison Control
Center right away.

PREGNANCY OR BREAST FEEDING

If pregnant or breastfeeding, ask a
health professional before use.

Other information
Do not use if inner seal is missing or
broken.
Store in a cool, dry place.

Inactive ingredients
Cetostearyl alcohol, glycerin, purified water

Directions
Adults: Apply a small amount on the affected
area in the morning and at night for one month,
or as recommended by your healthcare
practitioner. Cover with a bandage after each
application.

Children: Use under the direction
of your healthcare practitioner

Uses
For the temporary relief of external warts.

Directions
Adults: Apply a small amount on the affected
area in the morning and at night for one month,
or as recommended by your healthcare
practitioner. Cover with a bandage after each
application.

Children: Use under the direction
of your healthcare practitioner.

PACKAGE LABEL

NDC 62106-1179-0

UNDA topicals

CHELIDERM CREAM

Homeopathic Preparation

For the temporary relief of external warts.

Net Weight 1.4 oz (40 g)